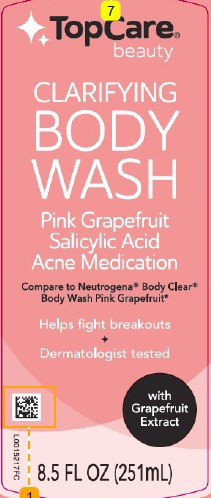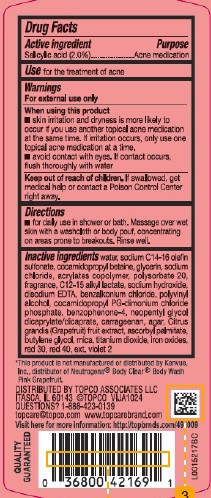 DRUG LABEL: Body Wash
NDC: 36800-354 | Form: GEL
Manufacturer: Topco Associates LLC
Category: otc | Type: HUMAN OTC DRUG LABEL
Date: 20260213

ACTIVE INGREDIENTS: SALICYLIC ACID 20 mg/1 mL
INACTIVE INGREDIENTS: WATER; SODIUM C14-16 OLEFIN SULFONATE; COCAMIDOPROPYL BETAINE; GLYCERIN; SODIUM CHLORIDE; BUTYL ACRYLATE/METHYL METHACRYLATE/METHACRYLIC ACID COPOLYMER (18000 MW); POLYSORBATE 20; C12-15 ALKYL LACTATE; SODIUM HYDROXIDE; EDETATE DISODIUM; BENZALKONIUM CHLORIDE; POLYVINYL ALCOHOL, UNSPECIFIED; COCAMIDOPROPYL PROPYLENE GLYCOL-DIMONIUM CHLORIDE PHOSPHATE; SULISOBENZONE; NEOPENTYL GLYCOL DICAPRYLATE/DICAPRATE; CARRAGEENAN; AGAR, UNSPECIFIED; PUMMELO; ASCORBYL PALMITATE; BUTYLENE GLYCOL; MICA; TITANIUM DIOXIDE; FERRIC OXIDE RED; D&C RED NO. 30; FD&C RED NO. 40; EXT. D&C VIOLET NO. 2

Top Care 353.001/353AE
Clarifying Body Wash Pink Grapefruit

Active ingredient

Salicylic acid (2.0%)

Purpose

Acne medication

Use

for the treatment of acne

Warnings

For external use only

When using this product

- skin irritation and dryness is more likely to occur if you use another topical acne medication at the same time. If irritation occurs, only use one topical acne medication at a time.
- avoid contact with the eyes. If contact occurs, flush thoroughly with water.

Keep out of reach of children.

If swallowed, get medical help or contact a Poison Control Center right away.

Directions

- for daily use in shower or bath. Massage over wet skin with a washcloth or body pouf, concentrating on areas prone to breakouts. Rinse well.

Inactive ingredients

water, sodium C14-16 olefin sulfonate, cocamidopropyl betaine, glycerin, sodium chloride, acrylates copolymer, polysorbate 20, fragrance, C12-15 alkyl lactate, sodium hydroxide, disodium EDTA, benzalkonium chloride, polyvinyl alcohol, cocamidopropyl PG-dimonium chloride phosphate, benzophenone-4, neopentyl glycol dicaprylate/dicaprate, carrageenan, agar, Citrus grandis (Grapefruit) fruit extract, ascorbyl palmitate, butylene glycol, mica, titanium dioxide, iron oxides, red 30, red 40, ext. violet 2

Disclaimer

*This product is not manufactured or distributed by Kenvue, Inc., distributor of Neutrogena®Body Clear®Body Wash Pink Graperfuit.

ADVERSE REACTION

Distributed by Topco Associates LLC

Itasca, IL 60143 ©TOPCO VIJA1024

Questions? 1-888-423-0139

topcare@topco.comwww.topcarebrand.com

Visit here for more information: http://topbrnds.com/491009

QUALITY GUARANTEED

Principal Display Panel

TopCare®

beauty

CLARIFYING BODY WASH

Pink Grapefruit

Salicylic Acid

Acne Medication

Compare to Neutrogena®Body Clear®Body Wash Pink Grapefruit*

Helps fight body breakouts

Dermatologist tested

with Grapefuit Extract

8.5 FL OZ (251 mL)